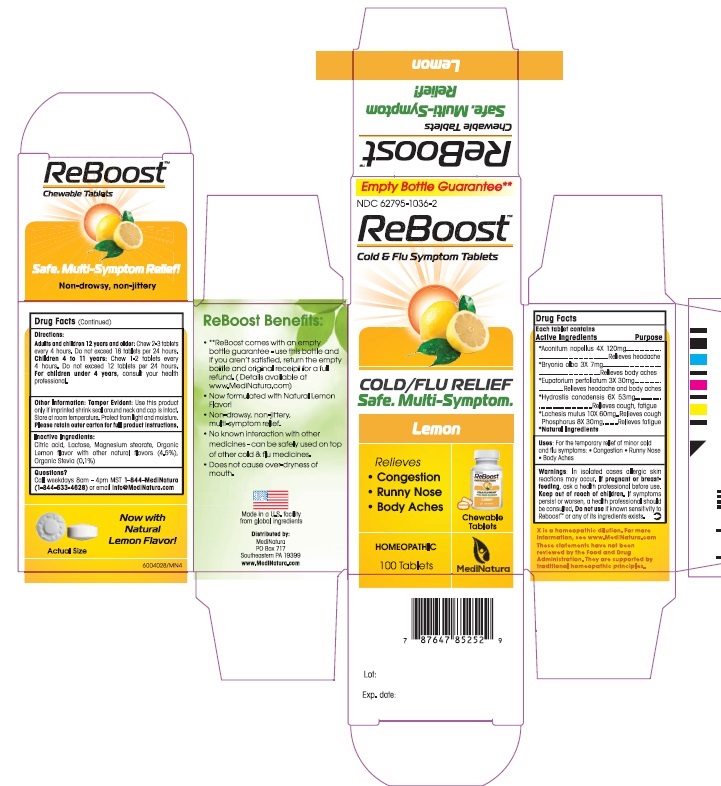 DRUG LABEL: ReBoost Lemon Flu Symptom Relief
NDC: 62795-1036 | Form: TABLET, CHEWABLE
Manufacturer: MediNatura Inc
Category: homeopathic | Type: HUMAN OTC DRUG LABEL
Date: 20181017

ACTIVE INGREDIENTS: ACONITUM NAPELLUS 4 [hp_X]/1 1; GOLDENSEAL 6 [hp_X]/1 1; EUPATORIUM PERFOLIATUM FLOWERING TOP 3 [hp_X]/1 1; LACHESIS MUTA VENOM 10 [hp_X]/1 1; PHOSPHORUS 8 [hp_X]/1 1; ANHYDROUS CITRIC ACID 8 [hp_X]/1 1; BRYONIA ALBA ROOT 3 [hp_X]/1 1
INACTIVE INGREDIENTS: MAGNESIUM STEARATE 1 g/1 1; LACTOSE 1 g/1 1; STEVIA LEAF 1 g/1 1

ReBoost Cold and Flu Symptom Relief Lemon Tablet

KEET OUT OF REACH OF CHILDREN

USES

For the temporary relief of minor cold and flu symptoms: • Congestion •Runny Nose •Body Aches

WARNINGS

In isolated cases allergic skin reactions may occur. If pregnant or breastfeeding, ask a health professional before use. Keep out of reach of children. If symptoms persist or worsen, a health professional should be consulted. Do not use if known sensitivity to Reboost™ or any of its ingredients exists.

DIRECTIONS

At first sign of symptoms:

Adults and children 12 years and older: Chew 2-3 tablets every 4 hours. Do not exceed 18 tablets in 24 hours.

Children 4 to 11 years: Chew 1-2 tablets every 4 hours. Do not exceed 18 tablets in 24 hours.

For children under 4 years, consult your health professional.

Allow tablets to dissolve completely in the mouth.

ACTIVE INGREDIENTS

*Aconitum napellus 4X, *Bryonia alba 3X*Bryonia alba 3X, *Eupatorium perfoliatum 3X,*Hydrastis canadensis 6X, *Lachesis mutus 10X, and Phosphorus 5X

*Natural Ingredients

INACTIVE INGREDIENTS

Citric acid, Lactose, Magnesium stearate, Organic Lemon flavor with other natural flavors (4.5%), Organic Stevia (0.1%)

Purpose

Relieves

• Congestion

• Runny Nose

• Body Aches